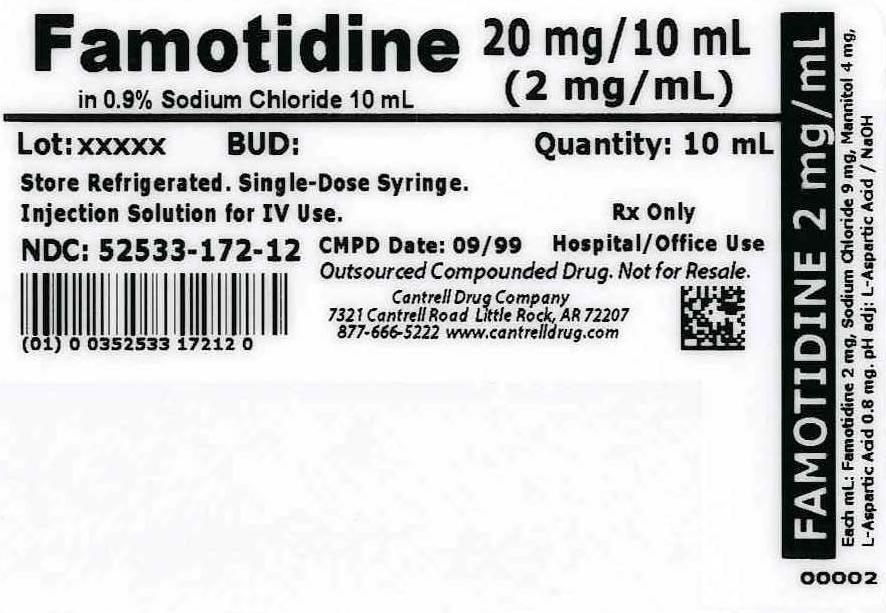 DRUG LABEL: Famotidine
NDC: 52533-172 | Form: INJECTION, SOLUTION
Manufacturer: Cantrell Drug Company
Category: prescription | Type: HUMAN PRESCRIPTION DRUG LABEL
Date: 20140616

ACTIVE INGREDIENTS: FAMOTIDINE 2 mg/1 mL
INACTIVE INGREDIENTS: SODIUM CHLORIDE 9 mg/1 mL; MANNITOL 4 mg/1 mL; ASPARTIC ACID 0.005 mg/1 mL; WATER

Famotidine 2 mg/mL in 0.9% Sodium Chloride 10 mL Syringe